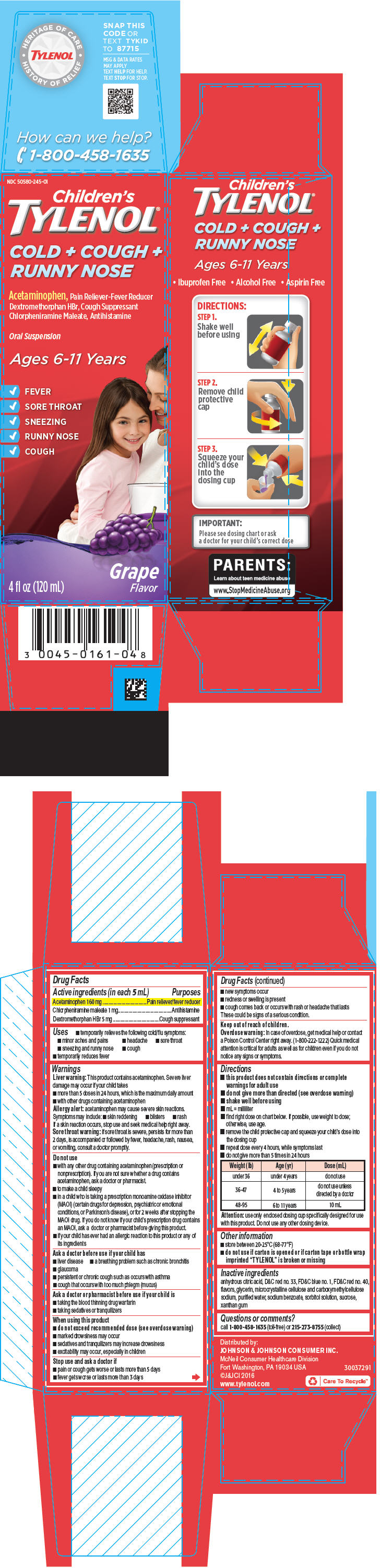 DRUG LABEL: Childrens TYLENOL
NDC: 50580-245 | Form: SUSPENSION
Manufacturer: Kenvue Brands LLC
Category: otc | Type: HUMAN OTC DRUG LABEL
Date: 20250218

ACTIVE INGREDIENTS: ACETAMINOPHEN 160 mg/5 mL; CHLORPHENIRAMINE MALEATE 1 mg/5 mL; DEXTROMETHORPHAN HYDROBROMIDE 5 mg/5 mL
INACTIVE INGREDIENTS: FD&C BLUE NO. 1; ANHYDROUS CITRIC ACID; FD&C RED NO. 40; MICROCRYSTALLINE CELLULOSE; GLYCERIN; CARBOXYMETHYLCELLULOSE SODIUM, UNSPECIFIED FORM; WATER; SODIUM BENZOATE; SORBITOL SOLUTION; SUCROSE; XANTHAN GUM; D&C RED NO. 33

Children's TYLENOL® COLD + COUGH + RUNNY NOSE

Drug Facts

ACTIVE INGREDIENT

PURPOSE

Active ingredients (in each 5 mL) | Purposes
Acetaminophen 160 mg | Pain reliever/fever reducer
Chlorpheniramine maleate 1 mg | Antihistamine
Dextromethorphan HBr 5 mg | Cough suppressant

Uses

- temporarily relieves the following cold/flu symptoms:
  - minor aches and pains
  - headache
  - sore throat
  - sneezing and runny nose
  - cough
- temporarily reduces fever

Warnings

Liver warning

This product contains acetaminophen. Severe liver damage may occur if your child takes

- more than 5 doses in 24 hours, which is the maximum daily amount
- with other drugs containing acetaminophen

Allergy alert: acetaminophen may cause severe skin reactions.

Symptoms may include:

- skin reddening
- blisters
- rash

If a skin reaction occurs, stop use and seek medical help right away.

Sore throat warning: if sore throat is severe, persists for more than 2 days, is accompanied or followed by fever, headache, rash, nausea, or vomiting, consult a doctor promptly.

Do not use

- with any other drug containing acetaminophen (prescription or nonprescription). If you are not sure whether a drug contains acetaminophen, ask a doctor or pharmacist.
- to make a child sleepy
- in a child who is taking a prescription monoamine oxidase inhibitor (MAOI) (certain drugs for depression, psychiatric or emotional conditions, or Parkinson's disease), or for 2 weeks after stopping the MAOI drug. If you do not know if your child's prescription drug contains an MAOI, ask a doctor or pharmacist before giving this product.
- if your child has ever had an allergic reaction to this product or any of its ingredients

Ask a doctor before use if your child has

- liver disease
- a breathing problem such as chronic bronchitis
- glaucoma
- persistent or chronic cough such as occurs with asthma
- cough that occurs with too much phlegm (mucus)

Ask a doctor or pharmacist before use if your child is

- taking the blood thinning drug warfarin
- taking sedatives or tranquilizers

When using this product

- do not exceed recommended dose (see overdose warning)
- marked drowsiness may occur
- sedatives and tranquilizers may increase drowsiness
- excitability may occur, especially in children

Stop use and ask a doctor if

- pain or cough gets worse or lasts more than 5 days
- fever gets worse or lasts more than 3 days
- new symptoms occur
- redness or swelling is present
- cough comes back or occurs with rash or headache that lasts

These could be signs of a serious condition.

Keep out of reach of children.

Overdose warning

In case of overdose, get medical help or contact a Poison Control Center right away. (1-800-222-1222) Quick medical attention is critical for adults as well as for children even if you do not notice any signs or symptoms.

Directions

- this product does not contain directions or complete warnings for adult use
- do not give more than directed (see overdose warning)
- shake well before using
- mL = milliliter
- find right dose on chart below. If possible, use weight to dose; otherwise, use age.
- remove the child protective cap and squeeze your child's dose into the dosing cup
- repeat dose every 4 hours, while symptoms last
- do not give more than 5 times in 24 hours

Weight (lb) | Age (yr) | Dose (mL)
under 36 | under 4 years | do not use
36-47 | 4 to 5 years | do not use unless directed by a doctor
48-95 | 6 to 11 years | 10 mL

Attention: use only enclosed dosing cup specifically designed for use with this product. Do not use any other dosing device.

Other information

- store between 20-25°C (68-77°F)
- do not use if carton is opened or if carton tape or bottle wrap imprinted "TYLENOL" is broken or missing

Inactive ingredients

anhydrous citric acid, D&C red no. 33, FD&C blue no. 1, FD&C red no. 40, flavors, glycerin, microcrystalline cellulose and carboxymethylcellulose sodium, purified water, sodium benzoate, sorbitol solution, sucrose, xanthan gum

Questions or comments?

call 1-800-458-1635 (toll-free) or 215-273-8755 (collect)

PRINCIPAL DISPLAY PANEL

NDC 50580-245-01

Children's
TYLENOL®

COLD + COUGH +
RUNNY NOSE

Acetaminophen, Pain Reliever-Fever Reducer
Dextromethorphan HBr, Cough Suppressant
Chlorpheniramine Maleate, Antihistamine

Oral Suspension

Ages 6-11 Years

- FEVER
- SORE THROAT
- SNEEZING
- RUNNY NOSE
- COUGH

4 fl oz (120 mL)

Grape
Flavor